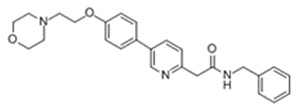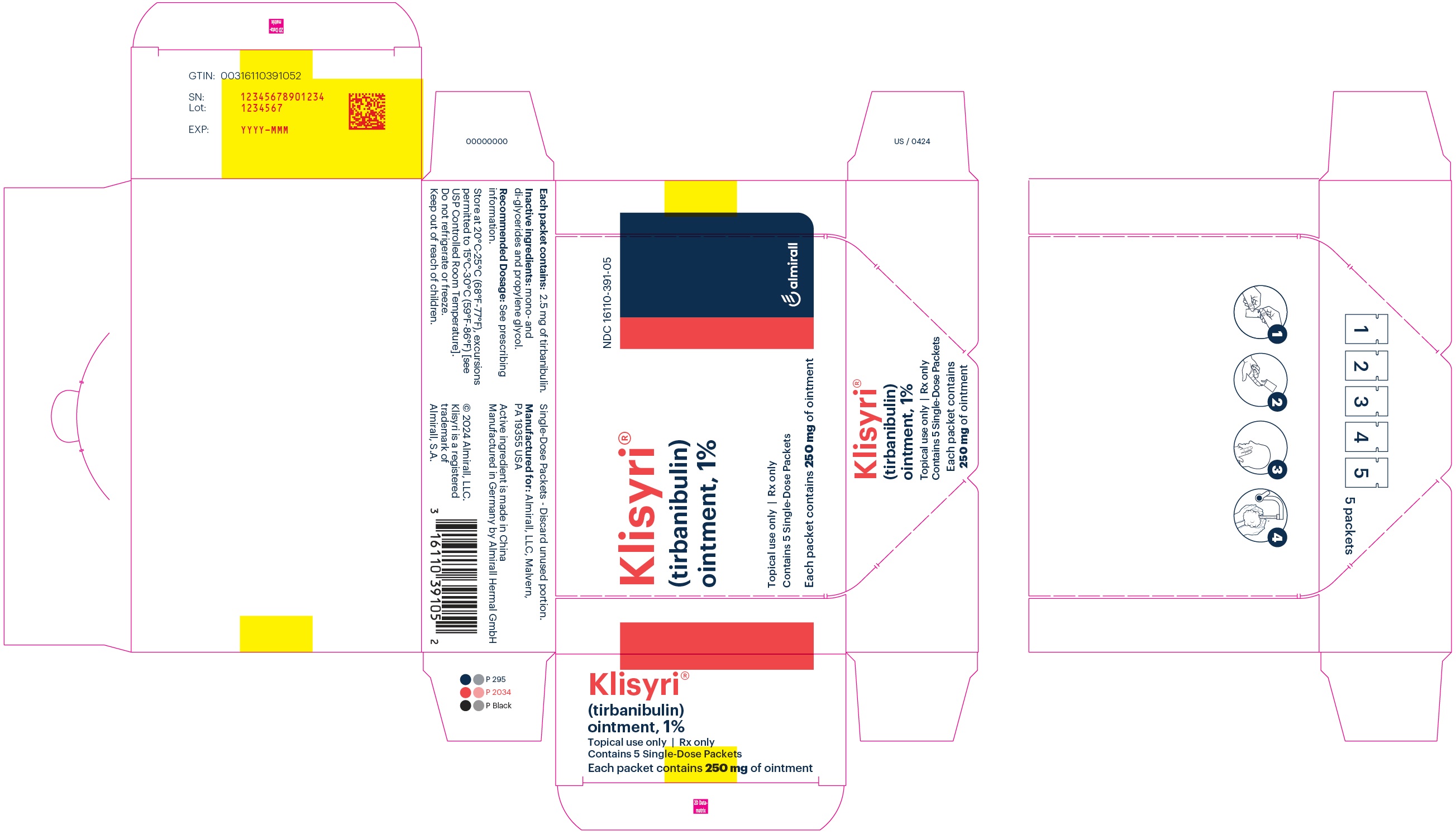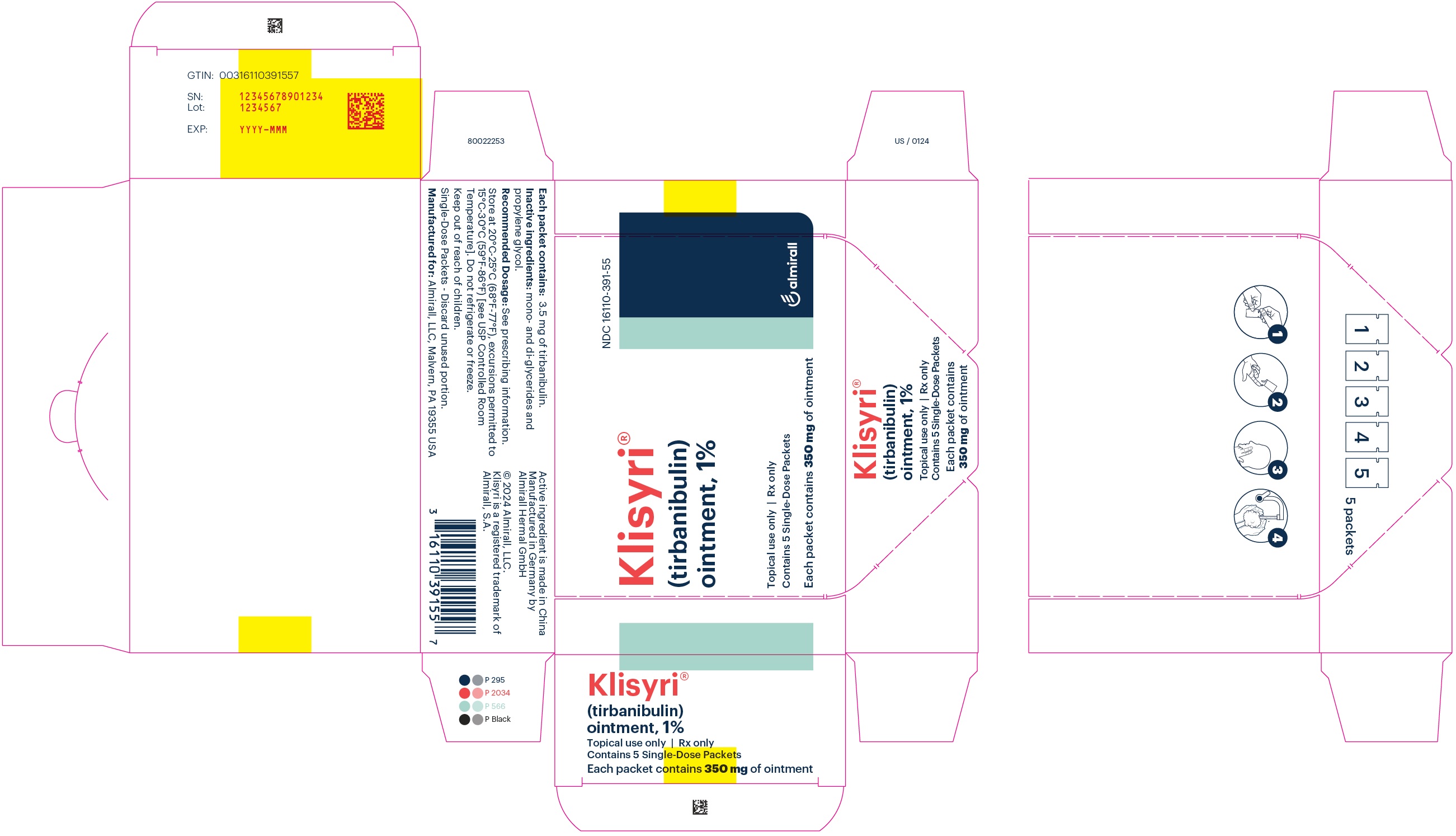 DRUG LABEL: Klisyri
NDC: 16110-391 | Form: OINTMENT
Manufacturer: Almirall, LLC
Category: prescription | Type: HUMAN PRESCRIPTION DRUG LABEL
Date: 20241108

ACTIVE INGREDIENTS: TIRBANIBULIN 10 mg/1 g
INACTIVE INGREDIENTS: GLYCERYL MONO AND DIPALMITOSTEARATE; PROPYLENE GLYCOL

HIGHLIGHTS OF PRESCRIBING INFORMATION

These highlights do not include all the information needed to use KLISYRI safely and effectively. See full prescribing information for KLISYRI.
KLISYRI (tirbanibulin) ointment, for topical use
Initial U.S. Approval: 2020

1 INDICATIONS AND USAGE

KLISYRI is a microtubule inhibitor indicated for the topical treatment of actinic keratosis of the face or scalp. (1)

2 DOSAGE AND ADMINISTRATION

- For topical use; not for oral or ophthalmic use. (2)
- Apply KLISYRI to the treatment field on the face or scalp once daily for 5 consecutive days using 1 unit-dose packet per application. (2)

3 DOSAGE FORMS AND STRENGTHS

Ointment: 1% tirbanibulin supplied in unit-dose packets. (3)

4 CONTRAINDICATIONS

None. (4)

5 WARNINGS AND PRECAUTIONS

- Ophthalmic Adverse Reactions: May cause eye irritation upon ocular exposure. Avoid transfer of the drug into the eyes and to the periocular area. If accidental exposure occurs, flush eyes with water and seek medical care. (5.1)
- Local Skin Reactions: Local skin reactions can occur including severe reactions (e.g., vesiculation/pustulation, erosion/ulceration) in the treated area. Avoid use until skin is healed from any previous drug or surgical treatment. (5.2)

6 ADVERSE REACTIONS

Most common adverse reactions (incidence ≥2%) are local skin reactions, application site pruritus, and application site pain. (6.1)

To report SUSPECTED ADVERSE REACTIONS, contact Almirall, at 1-866-665-2782 or FDA at 1-800-FDA-1088 or www.fda.gov/medwatch.

FULL PRESCRIBING INFORMATION

1 INDICATIONS AND USAGE

KLISYRI is indicated for the topical field treatment of actinic keratosis on the face or scalp.

2 DOSAGE AND ADMINISTRATION

For topical use only; not for oral or ophthalmic use.

Apply KLISYRI evenly to cover up to 100 cm^2 treatment field on the face or balding scalp once daily for 5 consecutive days using 1 unit-dose packet per application.

Wash hands immediately with soap and water after application.

Avoid washing and touching the treated area for approximately 8 hours after application of KLISYRI. Following this time, the area may be washed with a mild soap.

Avoid transfer of KLISYRI to the periocular area [see Warnings and Precautions (5.1)].

Avoid application near and around the mouth and lips.

3 DOSAGE FORMS AND STRENGTHS

Ointment: 1% white to off-white ointment supplied in a unit-dose packet (2.5 mg tirbanibulin in 250 mg or 3.5 mg tirbanibulin in 350 mg).

4 CONTRAINDICATIONS

None.

5 WARNINGS AND PRECAUTIONS

5.1 Ophthalmic Adverse Reactions

KLISYRI may cause eye irritation.

Avoid transfer of the drug into the eyes and to the periocular area during and after application. Wash hands immediately after application. If accidental exposure occurs, instruct patient to flush eyes with water and seek medical care as soon as possible.

5.2 Local Skin Reactions

Local skin reactions, including severe reactions (erythema, flaking/scaling, crusting, swelling, vesiculation/pustulation and erosion/ulceration) in the treated area can occur after topical application of KLISYRI [see Adverse Reactions (6.1)]. Occlusion after topical application of KLISYRI is more likely to result in irritation. Avoid use until skin is healed from any previous drug, procedure, or surgical treatment.

6 ADVERSE REACTIONS

6.1 Clinical Trials Experience

Because clinical trials are conducted under widely varying conditions, adverse reaction rates observed in the clinical trials of a drug cannot be directly compared to rates in the clinical trials of another drug and may not reflect the rates observed in clinical practice.

Two double-blind, vehicle-controlled clinical trials were conducted in 702 adult subjects with actinic keratosis on the face or scalp. Subjects were randomized 1:1 to KLISYRI or vehicle. Subjects enrolled in the trials had 4 to 8 clinically typical, visible, and discrete AK lesions in a contiguous area of 25 cm^2 on the face or scalp. Subjects’ average age was 70 years (range 45 to 96 years) and they were predominantly White (99%), male (87%), with Fitzpatrick skin types I or II (72%) and actinic keratosis on the face (68%) or scalp (32%). Treatment groups were comparable across all demographics and baseline characteristics, including AK lesion count and distribution on the face or scalp.

In the controlled trials, local skin reactions (LSRs) were collected independent of adverse events. Local skin reactions including erythema, flaking/scaling, crusting, swelling, vesiculation/pustulation, erosions/ulcerations were assessed by the investigators using a grading scale of 0 = absent, 1 = mild (slightly, barely perceptible), 2 = moderate (distinct presence), and 3 = severe (marked, intense).

The percentages of subjects with the maximal post-baseline grades for each local skin reaction (LSR) greater than baseline by treatment group are provided in Table 1. LSRs were mostly mild to moderate in severity (Table 1).

Table 1 Post-Baseline Local Skin Reactions in the Treatment Area (face or scalp) - Pooled Data from 2 Controlled Clinical Phase 3 Trials
 | KLISYRI N = 353 |  |  | Vehicle N = 349
Local Skin Reactions | Mild n (%) | Moderate n (%) | Severe n (%) | Mild n (%) | Moderate n (%) | Severe n (%)
Erythema | 76 (22%) | 223 (63%) | 22 (6%) | 98 (28%) | 20 (6%) | 0
Flaking/ Scaling | 92 (26%) | 166 (47%) | 31 (9%) | 86 (25%) | 33 (9%) | 1 (<1%)
Crusting | 107 (30%) | 50 (14%) | 7 (2%) | 31 (9%) | 8 (2%) | 0
Swelling | 102 (29%) | 32 (9%) | 2 (<1%) | 15 (4%) | 1 (<1%) | 0
Vesiculation/ Pustulation | 25 (7%) | 2 (<1%) | 2 (<1%) | 3 (<1%) | 0 | 0
Erosion/ Ulceration | 32 (9%) | 9 (3%) | 0 | 10 (3%) | 0 | 0

Table 2 presents the adverse reactions experienced in ≥2% of subjects participating in the controlled clinical trials with KLISYRI. No subject withdrew from the trials due to adverse reactions.

Table 2 Adverse Reactions Occurring in ≥2% of Subjects in 2 Controlled Clinical Trials– Pooled Safety Population
Adverse Reaction System Organ Class | KLISYRI N = 353 | Vehicle N = 349
Number of Subjects (%) with any adverse reaction (possibly related to treatment) | 56 (16%) | 35 (10%)
Application site pruritus | 32 (9%) | 21 (6%)
Application site paina | 35 (10%) | 11 (3%)
a Application site pain includes pain, tenderness, stinging, and burning sensation at the application site.

For the 51 subjects (45 KLISYRI, 6 vehicle) who maintained complete clearance through the 12-month follow-up period, no additional local adverse reactions were reported.

In a multicenter, open-label safety trial of 105 subjects where KLISYRI was applied to a treatment field of 100 cm^2 on the face or balding scalp, the results were comparable to the safety profile established by the controlled trials in subjects with a 25 cm^2 treatment area.

Dermal Safety Studies

Clinical studies in healthy subjects demonstrated KLISYRI did not cause contact sensitization (261 subjects), phototoxic skin reactions (31 subjects), or photoallergic skin reactions (64 subjects).

8 USE IN SPECIFIC POPULATIONS

8.1 Pregnancy

Risk Summary

There are no available data with KLISYRI use in pregnant women to evaluate for a drug-associated risk of major birth defects, miscarriage or adverse maternal or fetal outcomes.

In animal reproduction studies, oral administration of tirbanibulin to pregnant rats during the period of organogenesis resulted in an increased incidence of fetal deaths and malformations at a systemic exposure that was at least 19 times the exposure associated with the maximum recommended human dose (MRHD). Oral administration of tirbanibulin to pregnant rabbits during the period of organogenesis resulted in reduced mean fetal weight and size at a systemic exposure that was 41 times the exposure associated with the MRHD (see Data).

The background risk of major birth defects and miscarriage for the indicated population is unknown. All pregnancies have a background risk of birth defect, loss, or other adverse outcomes. In the U.S. general population, the estimated risk of major birth defects and miscarriage in clinically recognized pregnancies is 2 to 4% and 15 to 20%, respectively.

Data

Animal Data

Tirbanibulin induced fetal deaths and external, visceral, and skeletal malformations when administered orally to pregnant rats during the period of organogenesis at doses greater than or equal to 1.25 mg/kg/day, which resulted in systemic exposures at least 19 times the exposure associated with the MRHD on an Area Under the Curve (AUC) comparison basis. Tirbanibulin had no apparent effects on fetal development in rats at a dose of 0.5 mg/kg/day, which resulted in systemic exposures 5 times the exposure associated with the MRHD.

Tirbanibulin reduced mean fetal weight and size (crown-rump length) when administered orally to pregnant rabbits during the period of organogenesis at a dose of 3 mg/kg/day, which resulted in a systemic exposure 41 times the exposure associated with the MRHD on an AUC comparison basis. Tirbanibulin had no apparent effects on fetal development in rabbits at a dose of 1 mg/kg/day, which resulted in systemic exposures 14 times the exposure associated with the MRHD.

Tirbanibulin was assessed for effects on peri- and post-natal development of rats in a study that involved oral administration to pregnant rats during the period of organogenesis through lactation at dosages up to 1.25 mg/kg/day. These dosages resulted in systemic exposures up to 19 times the exposure associated with the MRHD on an AUC comparison basis. No adverse effects on maternal function or developmental, neurobehavioral, or reproductive performance of offspring were observed.

8.2 Lactation

Risk Summary

There are no data on lactational transfer of KLISYRI to human or animal milk. The effects of KLISYRI on the breastfed infant, or its effects on milk production, are unknown.

The developmental and health benefits of breastfeeding should be considered along with the mother’s clinical need for KLISYRI and any potential adverse effects on the breastfed child from tirbanibulin or from the underlying maternal condition.

8.4 Pediatric Use

The safety and effectiveness of KLISYRI for actinic keratosis in subjects less than 18 years of age have not been established. Actinic keratosis is not a condition generally seen within the pediatric population.

8.5 Geriatric Use

Of the 353 subjects with AK treated with KLISYRI in the 2 controlled Phase 3 trials, 246 (70%) were 65 years of age or older. No overall differences in safety or effectiveness were observed between these subjects and younger subjects, and other reported clinical experience has not identified differences in responses between the elderly and younger patients, but greater sensitivity of some older individuals cannot be ruled out.

11 DESCRIPTION

KLISYRI (tirbanibulin) ointment is a microtubule inhibitor for topical use. The chemical name of tirbanibulin is N-benzyl-2-(5-(4-(2-morpholinoethoxy)phenyl)pyridin-2-yl) acetamide. The molecular weight is 431.4 and the molecular formula is C26H29N3O3. Tirbanibulin’s structural formula is:

Tirbanibulin ointment 1% contains 10 mg tirbanibulin per gram of white to off-white ointment containing mono- and di-glycerides and propylene glycol.

12 CLINICAL PHARMACOLOGY

12.1 Mechanism of Action

Tirbanibulin is a microtubule inhibitor. The mechanism of action of KLISYRI for the topical treatment of actinic keratosis is unknown.

12.2 Pharmacodynamics

The pharmacodynamics of tirbanibulin in the treatment of actinic keratosis is unknown.

12.3 Pharmacokinetics

Absorption

Following topical treatment of a mean daily dose of 348 mg (range: 224 to 435 mg) of KLISYRI to a 100 cm^2 contiguous area of the face or balding scalp, once daily for 5 consecutive days. On Day 5, systemic exposure to tirbanibulin had a mean±SD maximum plasma concentration (Cmax) of 1.32±0.74 ng/mL and 0.71±0.31 ng/mL, and a mean±SD area under the plasma concentration from time zero to 24 hours (AUC24) of 19.6±8.1 h∗ng/mL and 11.7±4.4 h∗ng/mL, in subjects who received the face and scalp topical treatment, respectively. The median time to reach Cmax (Tmax) was ~6 hours.

Distribution

Plasma protein binding of tirbanibulin is 88% and is independent of concentrations in the range of 0.01 to 10 µg/mL.

Elimination

Metabolism

Following topical treatment with KLISYRI to adult subjects with actinic keratosis, the plasma concentrations of KX2-5036, KX2-5163, and KX2-5180, three pharmacologically inactive metabolites, were detectable with the highest plasma concentrations of 0.36 ng/mL, 0.42 ng/mL, and 1.70 ng/mL, respectively.

The in vitro study indicated that incubation of 1 or 10 µM tirbanibulin with human hepatocytes generated KX2-5036, KX2-5162 and other unidentified metabolites.

In vitro, tirbanibulin is mainly metabolized by CYP3A4, and to a lesser extent, CYP2C8.

Excretion

Excretion of tirbanibulin has not been fully characterized in humans.

Drug Interactions

Clinical Studies

No clinical studies evaluating the drug interaction potential of KLISYRI have been conducted.

In Vitro Studies

CYP Enzymes: Tirbanibulin and the metabolite KX2-5036 directly or time-dependently inhibited CYP 1A2, 2B6, 2C8, 2C9, 2C19, 2D6, or 3A4 with an IC50 value of >17 µM. Tirbanibulin up to 1 µM (431.5 ng/mL) and the metabolite KX2-5036 up to 3 µM (1024 ng/mL) did not induce CYP 1A2, 2B6, or 3A4. The metabolite KX2-5180 was neither an inhibitor of CYP1A2, 2B6, 2C8, 2C9, 2C19, 2D6 or 3A4 with an IC50 value of > 225 nM (85 ng/mL) nor an inducer of CYP1A2, 2B6, and 3A4 at a concentration of 225 nM (85 ng/mL). These findings suggest that KLISYRI has no clinically meaningful effect on the PK of drugs metabolized by CYP 1A2, 2B6, 2C8, 2C9, 2C19, 2D6, or 3A4.

Drug Transporters: Neither tirbanibulin nor the metabolite KX2-5036 was a substrate of MDR1, BCRP, BSEP, MRP2, MATE1, MATE2-K, OAT1, OAT3, OATP1B1, OATP1B3, OCT1 or OCT2. The metabolite KX2-5180 was a substrate of BCRP, but not a substrate for other transporters. Tirbanibulin and the metabolites of KX2-5036 and KX2-5180 inhibited MDR1, BCRP, MRP2, BSEP, MATE1, MATE2-K, OAT1, OTA3, OATP1B1, OATP1B3, OCT1 and/or OCT2 with an IC5050 value of >1 µM. The results suggest that KLISYRI has no clinically meaningful effect on the PK of drugs mediated by MDR1, BCRP, MRP2, BSEP, MATE1, MATE2-K, OAT1, OTA3, OATP1B1, OATP1B3, OCT1 and OCT2.

13 NONCLINICAL TOXICOLOGY

13.1 Carcinogenesis, Mutagenesis, Impairment of Fertility

No studies have been performed to evaluate the potential of tirbanibulin to induce carcinogenesis.

Tirbanibulin was negative in an in vitro bacterial reverse mutation (Ames) assay. Tirbanibulin was positive in an in vitro chromosomal aberration assay with Chinese hamster ovary (CHO) cells, an in vitro mouse lymphoma assay with L5178/TK+/- cells, and an in vivo micronucleus assay in rats.

Tirbanibulin was assessed for effects on fertility or reproductive function in rats. Reproductive performance of rats was unaffected by oral doses of tirbanibulin up to 4 mg/kg/day (24 times the MRHD on an AUC comparison basis) in males and 1 mg/kg/day (15 times the MRHD on an AUC comparison basis) in females. However, oral administration of 4 mg/kg/day of tirbanibulin to male rats adversely affected spermatogenesis, including reduced sperm count and motility, and increased observations of morphologically abnormal sperm. No effects on sperm were observed in males treated at 2 mg/kg/day (12 times the MRHD on an AUC comparison basis).

14 CLINICAL STUDIES

Actinic Keratosis of the Face or Scalp

Two double-blind, vehicle-controlled clinical trials (NCT03285477 and NCT03285490) were conducted with 702 adult subjects with actinic keratosis on the face or scalp. Subjects were randomized 1:1 to KLISYRI or vehicle. Subjects enrolled had 4 to 8 clinically typical, visible, and discrete AK lesions in a contiguous area of 25 cm^2 on the face or scalp. Subjects had an average age of 70 years (range 45 to 96 years), were predominantly White (99%), male (87%), with Fitzpatrick skin types I or II (72%) and actinic keratosis on the face (68%) or scalp (32%). Treatment groups were comparable across all demographics and baseline characteristics, including AK lesion count and distribution on the face or scalp.

Subjects received 5 consecutive days of once daily treatment with either KLISYRI (353) or vehicle control (349) to the treatment field. Subjects with complete (100%) clearance of AK lesions in the treatment area at Day 57 returned to the clinic for recurrence assessment every 3 months for a total of 12 months post-Day 57.

The primary efficacy endpoint was complete (100%) clearance of AK lesions in the treatment area, defined as the proportion of subjects at Day 57 with no clinically visible AK lesions in the treatment area and the secondary endpoint was partial (≥75%) clearance of AK lesions in the treatment area. Results from both trials are presented below.

Table 3 Complete (100%) AK Clearance Rates on Day 57 in Adults with AK on the Face or Scalp for the Two Phase 3 Trials (Intent to Treat [ITT] Population)
 | Study 1 |  |  |  | Study 2
 | KLISYRI N = 175 n/N (%) | Vehicle N = 176 n/N (%) | Treatment difference (KLISYRI-Vehicle) | 95% Confidence Interval for the Treatment difference | KLISYRI N = 178 n/N (%) | Vehicle N = 173 n/N (%) | Treatment difference (KLISYRI-Vehicle) | 95% Confidence Interval for the Treatment difference
All subjects | 77/175 (44%) | 8/176 (5%) | 40%a | (31.6%, 47.5%)a | 97/178 (54%) | 22/173 (13%) | 42%a | (33.1%, 50.7%)a
Face | 60/119 (50%) | 7/121 (6%) | 45% | -- | 73/119 (61%) | 16/118 (14%) | 48% | --
Scalp | 17/56 (30%) | 1/55 (2%) | 29% | -- | 24/59 (41%) | 6/55 (11%) | 30% | --
a. Based on Mantel-Haenszel method

Table 4 Partial (≥ 75%) AK Clearance Rates on Day 57 in Adults with AK on the Face or Scalp for the Two Phase 3 Trials (Intent to Treat [ITT] Population)
 | Study 1 |  |  |  | Study 2
 | KLISYRI N = 175 n/N (%) | Vehicle N = 176 n/N (%) | Treatment difference (KLISYRI-Vehicle) | 95% Confidence Interval for the Treatment difference | KLISYRI N = 178 n/N (%) | Vehicle N = 173 n/N (%) | Treatment difference (KLISYRI-Vehicle) | 95% Confidence Interval for the Treatment difference
All subjects | 119/175 (68%) | 29/176 (16%) | 52%a | (42.9%, 60.3%)a | 136/178 (76%) | 34/173 (20%) | 57% a | (48.3%, 65.4%)a
Face | 90/119 (76%) | 23/121 (19%) | 57% | -- | 95/119 (80%) | 26/118 (22%) | 58% | --
Scalp | 29/56 (52%) | 6/55 (11%) | 41% | -- | 41/59 (69%) | 8/55 (15%) | 55% | --
a. Based on Mantel-Haenszel method

Efficacy was consistent across sex and age (<65 and ≥65 years) subgroups.

Subjects who achieved 100% clearance of AK lesions in the treatment area at Day 57 continued to be followed for up to 12 months following Day 57 to determine the recurrence rate. Recurrence was defined as the proportion of subjects with any identified AK lesion (new or previous lesion) in the previously treated area who achieved 100% clearance at Day 57. Of the 174 subjects treated with KLISYRI who were followed, the recurrence rate at 12 months post-Day 57 was 73%.

16 HOW SUPPLIED/STORAGE AND HANDLING

KLISYRI is a white to off-white ointment and is supplied in unit-dose packets containing either 250 mg or 350 mg of tirbanibulin ointment 1%. Discard each unit-dose packet after use.

NDC 16110-391-05 (5 unit-dose packets each containing 250 mg of ointment)
NDC 16110-391-55 (5 unit-dose packets each containing 350 mg of ointment)

STORAGE AND HANDLING

Store at 20°C-25°C (68°F-77°F), excursions permitted to 15°C-30°C (59°F-86°F) [see USP Controlled Room Temperature]. Do not refrigerate or freeze.

17 PATIENT COUNSELING INFORMATION

Advise the patient to read the FDA-approved patient labeling (Patient Information and Instructions for Use).

Ophthalmic Adverse Reactions

Advise patients that KLISYRI is not for ophthalmic use. Advise patients to avoid application around the eyes, and transfer of the drug into the eyes and to the periocular area. If accidental exposure occurs, advise patients to flush eyes with water and seek medical care [see Warnings and Precautions (5.1)].

Local Skin Reactions

Inform patients that treatment with KLISYRI may lead to local skin reactions [see Warnings and Precautions (5.2)].

Important Administration Instructions

Advise patients that KLISYRI is for topical use only. Advise patients to avoid application near and around the eyes, mouth and lips.

Instruct patients to:

- Wash hands well after applying KLISYRI to avoid transfer of the drug into the eyes and to the periocular area after application.
- Avoid washing and touching the treated area for 8 hours after treatment. Following this time, patients may wash the area with a mild soap and water [see Dosage and Administration (2)].
- Avoid inadvertent transfer of KLISYRI to other areas, or to another person.

Manufactured for: Almirall, LLC
Malvern, PA. 19355, USA

Patient Information

KLISYRI (klye si' ree)
(tirbanibulin)
ointment

Important: KLISYRI is for use on the skin only (topical). Do not use KLISYRI in, around, or near your eyes, mouth or lips.

What is KLISYRI?

KLISYRI is a prescription medicine used on the skin to treat actinic keratosis on the face or scalp.

It is not known if KLISYRI is safe and effective in children less than 18 years of age.

Before using KLISYRI, tell your healthcare provider about all of your medical conditions, including if you:

- are being treated or have been treated for actinic keratosis with any other medicine, procedure, or surgery. You should not use KLISYRI until your skin has healed from other treatments.
- have other skin problems in the treatment area.
- are pregnant or plan to become pregnant. It is not known if KLISYRI can harm your unborn baby.
- are breastfeeding or plan to breastfeed. It is not known if KLISYRI passes into your breast milk. Talk to your healthcare provider about the best way to feed your baby during treatment with KLISYRI.

Tell your healthcare provider about all the medicines you take, including prescription and over-the-counter medicines, vitamins and herbal supplements.

How should I use KLISYRI?

- Use KLISYRI as your healthcare provider tells you to. KLISYRI is for skin use only.
- Apply KLISYRI to evenly cover the treatment area(s) on the face or scalp 1 time a day for 5 days in a row (consecutive) using 1 single dose packet with each application. Do not apply KLISYRI to other areas.
- Do not use more KLISYRI than you need to cover the treatment area. Using too much KLISYRI, or using it too often, or for too long can increase your chances of having a severe skin reaction or other side effects.
- Do not cover the treatment area with a dressing after application of KLISYRI. Irritation of the skin may happen if a dressing is applied to the treatment area.
- Do not get KLISYRI in, around, or near your eyes. Do not touch your eyes while you are applying KLISYRI.
  - Wash your hands right away with water and soap after applying KLISYRI. After applying KLISYRI, be careful to keep KLISYRI on the treated area from coming into contact with your eyes. Irritation may happen if you get KLISYRI in your eyes.
  - If you accidently get KLISYRI in your eyes, flush them with water and get medical care as soon as possible. See, “What are the possible side effects of KLISYRI?”
- Do not get KLISYRI in, around, or near your mouth or lips.
- Avoid washing and touching the treated area for approximately 8 hours after application of KLISYRI. After 8 hours, you may wash the area with a mild soap and water.
- Avoid transferring the product to other areas after application.
- Throw away any open packet of KLISYRI after use even if there is medicine still left in it.

What are the possible side effects of KLISYRI?

KLISYRI may cause serious side effects, including:

- Eye irritation can happen if KLISYRI gets into your eyes. If you accidently get KLISYRI into your eyes, flush them with water and get medical care as soon as possible.
- Local skin reactions are common but can also be severe during treatment with KLISYRI. Call your healthcare provider if you develop any local skin reactions including redness, flaking or scaling, crusting, or swelling that is more severe, or if you get blisters, peeling, pus, ulcers, or breakdown of your skin.

The most common side effects of KLISYRI include: itching or pain in the treatment area.

These are not all of the possible side effects of KLISYRI. Call your doctor for medical advice about side effects. You may report side effects to FDA at 1-800-FDA-1088.

How should I store KLISYRI?

- Store at room temperature between 68°F to 77°F (20°C to 25°C) .
- Do not refrigerate or freeze.
- Safely throw away used KLISYRI packets in household trash.
- Keep KLISYRI and all medicines out of the reach of children.

General Information about the safe and effective use of KLISYRI.

Medicines are sometimes prescribed for purposes other than those listed in a Patient Information leaflet. Do not use KLISYRI for a condition for which it was not prescribed. Do not give KLISYRI to other people, even if they have the same symptoms you have. It may harm them. You can ask your pharmacist or healthcare provider for information about KLISYRI that is written for health professionals.

What are the ingredients of KLISYRI?

Active ingredient: Tirbanibulin

Inactive ingredients: Mono- and di-glycerides and propylene glycol.

Manufactured for: Almirall, LLC, Malvern, PA. 19355, USA.

For more information, call 1-800-KLISYRI or visit www.KLISYRI.com.

This Patient Information has been approved by the U.S. Food and Drug Administration.

Issued: 08/2021